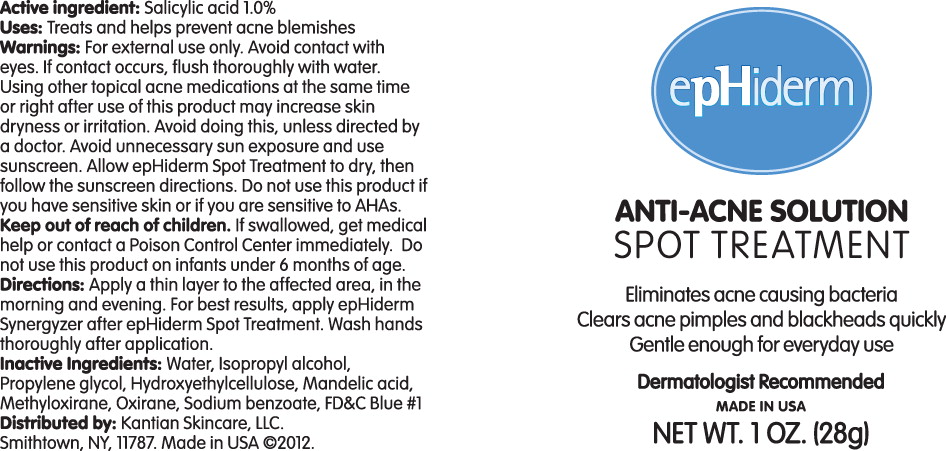 DRUG LABEL: epHiderm Spot Treatment
NDC: 57524-013 | Form: LOTION
Manufacturer: KANTIAN SKINCARE, LLC
Category: otc | Type: HUMAN OTC DRUG LABEL
Date: 20130404

ACTIVE INGREDIENTS: Salicylic Acid 1.0 mg/1 g
INACTIVE INGREDIENTS: Water; Isopropyl Alcohol; Propylene Glycol; HYDROXYETHYL CELLULOSE (2000 MPA.S AT 1%); Mandelic Acid; Sodium Benzoate; FD&C Blue No. 1; Propylene Oxide

Active Ingredient:

Salicylic acid 1.0%

Uses:

Treats and helps prevent acne blemishes

Warnings:

For external use only. Avoid contact with eyes. If contact occurs, flush thoroughly with water. Using other topical acne medications at the same time or right after use of this product may increase skin dryness or irritation. Avoid doing this, unless directed by a doctor. Avoid unnecessary sun exposure and use sunscreen. Allow epHiderm Spot Treatment to dry, then follow the sunscreen directions. Do not use this product if you have sensitive skin or if you are sensitive to AHAs.

Keep out of reach of children. If swallowed, get medical help or contact a Poison Control Center immediately. Do not use this product on infants under 6 months of age.

Directions:

Apply a thin layer to the affected area, In the morning and evening. For best results, apply epHiderm Synergyzer after epHiderm Spot Treatment. Wash hands thoroughly after application.

Inactive Ingredients:

Water, Isopropyl alcohol, Propylene glycol, Hydroxyethylcellulose, Mandelic acid, Methyloxirane, Oxirane, Sodium benzoate, FD&C Blue #1

Distributed by: Kantian Skincare, LLC.
Smithtown, NY, 11787. Made in USA ©2012.

Principal Display Panel – Tube Label

epHiderm

ANTI-ACNE SOLUTION
SPOT TREATMENT

Eliminates acne causing bacteria
Clears acne pimples and blackheads quickly
Gentle enough for everyday use

Dermatologist Recommended

MADE IN USA

NET WT. 1 OZ (28g)